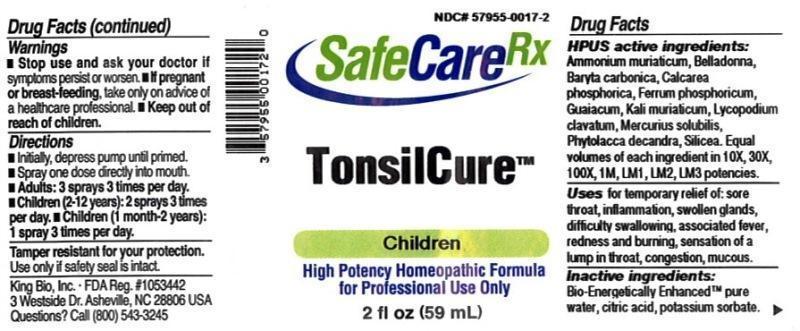 DRUG LABEL: TonsilCure
NDC: 57955-0017 | Form: LIQUID
Manufacturer: King Bio Inc.
Category: homeopathic | Type: HUMAN OTC DRUG LABEL
Date: 20150320

ACTIVE INGREDIENTS: AMMONIUM CHLORIDE 10 [hp_X]/59 mL; BARIUM CARBONATE 10 [hp_X]/59 mL; ATROPA BELLADONNA 10 [hp_X]/59 mL; TRIBASIC CALCIUM PHOSPHATE 10 [hp_X]/59 mL; FERROSOFERRIC PHOSPHATE 10 [hp_X]/59 mL; GUAIACUM OFFICINALE RESIN 10 [hp_X]/59 mL; POTASSIUM CHLORIDE 10 [hp_X]/59 mL; LYCOPODIUM CLAVATUM SPORE 10 [hp_X]/59 mL; MERCURIUS SOLUBILIS 10 [hp_X]/59 mL; PHYTOLACCA AMERICANA ROOT 10 [hp_X]/59 mL; SILICON DIOXIDE 10 [hp_X]/59 mL
INACTIVE INGREDIENTS: WATER; ANHYDROUS CITRIC ACID; POTASSIUM SORBATE

TonsilCure™

ACTIVE INGREDIENT

Drug Facts__________________________________________________________________________________________________________

HPUS active ingredients: Ammonium muriaticum, Baryta carbonica, Belladonna, Calcarea phosphorica, Ferrum phosphoricum, Guaiacum, Kali Muriaticum, Lycopodium clavatum, Mercurius solubilis, Phytolacca decandra, Silicea. Equal volumes of each ingredient in 10X, 30X, 100X, 1M, LM1, LM2, LM3 potencies.

INDICATIONS AND USAGE

Uses for temporary relief of: sore throat, inflammation, swollen glands, difficulty swallowing, associated fever, redness and burning, sensation of a lump in throat, congestion, mucous.

Inactive Ingredients:

Bio-Energetically Enhanced™ pure water, citric acid and potassium sorbate.

Warnings

- Stop use and ask your doctor if symptoms persist or worsen.
- If pregnant or breast-feeding, take only on advice of a healthcare professional.

- Keep out of reach of children.

Directions

- Initially, depress pump until primed.
- Spray one dose directly into mouth.
- Adults: 3 sprays 3 times per day
- Children (2-12 years): 2 sprays 3 times per day
- Children(1moth-2 years): 1 spray 3 times per day

OTHER SAFETY INFORMATION

Tamper resistant for your protection. Use only if safety seal is intact.

PURPOSE

Uses for temporary relief of:

- sore throat
- inflammation
- swollen glands
- difficulty swallowing
- associated fever
- redness and burning
- sensation of a lump in throat, congestion, mucous